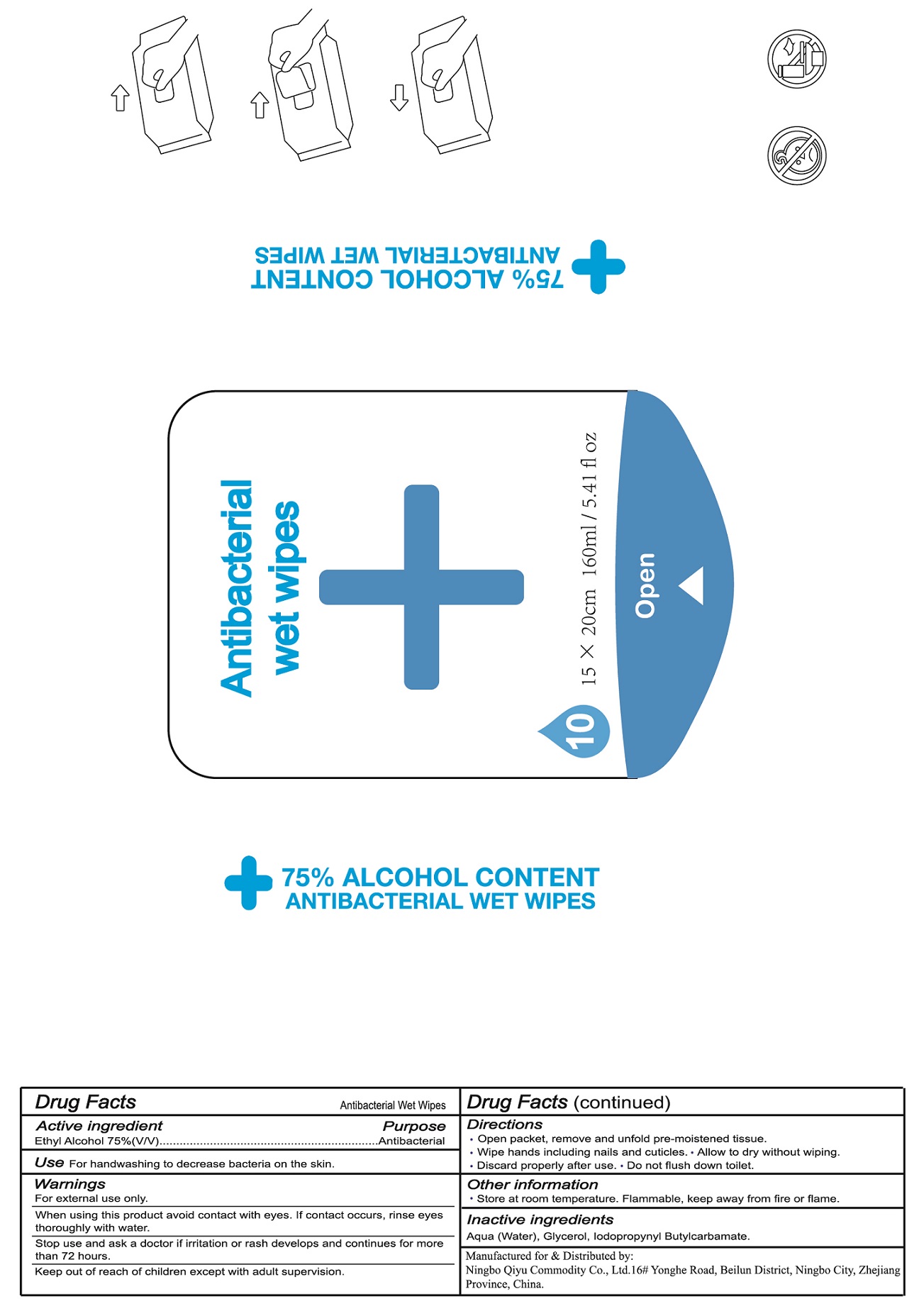 DRUG LABEL: Antibacterial Wet Wipes
NDC: 76562-003 | Form: CLOTH
Manufacturer: Ningbo Qiyu Commodity Co., Ltd.
Category: otc | Type: HUMAN OTC DRUG LABEL
Date: 20200518

ACTIVE INGREDIENTS: ALCOHOL 0.75 mL/1 mL
INACTIVE INGREDIENTS: WATER; GLYCERIN; IODOPROPYNYL BUTYLCARBAMATE

Antibacterial Wet Wipes, 10ct

Active ingredient

Ethyl Alcohol 75% (V/V)

Purpose

Antibacterial

Use

For handwashing to decrease bacteria on the skin.

Warnings

For external use only.

When using this product

avoid contact with eyes. If contact occurs, rinse eyes thoroughly with water.

Stop use and ask a doctor

if irritation or rash develops and continues for more than 72 hours.

Keep out of reach of children

except with adult supervision.

Directions

- Open packet, remove and unfold pre-moistened tissue.
- Wipe hands including nails and cuticles.
- Allow to dry without wiping.
- Discard properly after use.
- Do not flush down toilet.

Other information

- Store at room temperature, Flammable, keep away from fire or flame.

Inactive ingredients

Aqua (Water), Glycerol, Iodopropynyl Butylcarbamate.